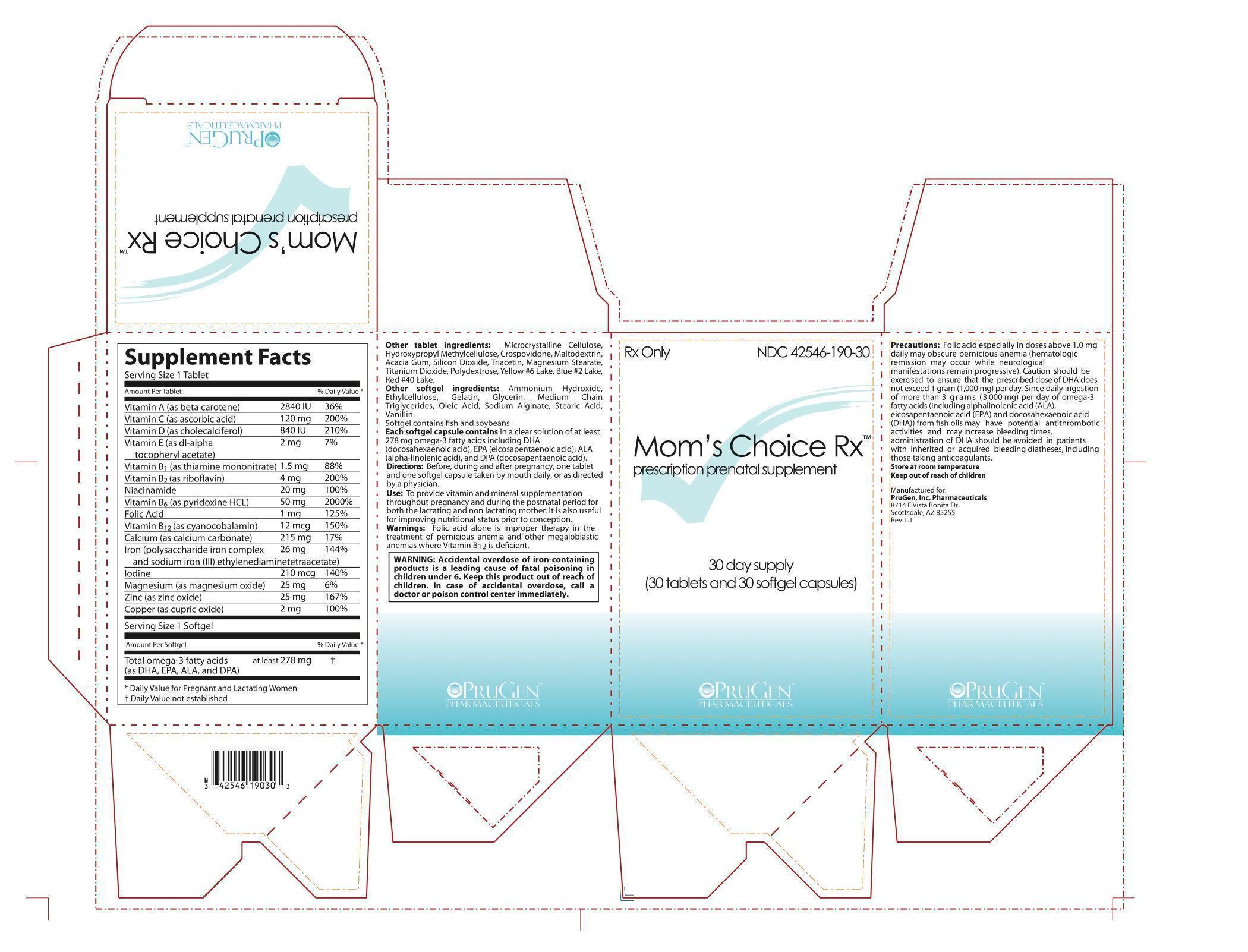 DRUG LABEL: Moms Choice Rx
NDC: 42546-190 | Form: KIT | Route: ORAL
Manufacturer: PruGen, Inc.
Category: prescription | Type: HUMAN PRESCRIPTION DRUG LABEL
Date: 20130401

ACTIVE INGREDIENTS: BETA CAROTENE 2840 [iU]/1 1; ASCORBIC ACID 120 mg/1 1; CHOLECALCIFEROL 840 [iU]/1 1; .ALPHA.-TOCOPHEROL ACETATE, D- 2 mg/1 1; THIAMINE 1.5 mg/1 1; RIBOFLAVIN 4 mg/1 1; NIACINAMIDE 20 mg/1 1; PYRIDOXINE HYDROCHLORIDE 50 mg/1 1; FOLIC ACID 1 mg/1 1; CYANOCOBALAMIN .012 mg/1 1; CALCIUM CARBONATE 215 mg/1 1; IRON 26 mg/1 1; MAGNESIUM 25 mg/1 1; ZINC OXIDE 25 mg/1 1; CUPRIC CATION 2 mg/1 1; IODINE .223 mg/1 1; OMEGA-3 FATTY ACIDS 278 mg/1 1

Mom's Choice Rx

DESCRIPTION

SUPPLEMENT FACTS
Serving Size 1 Tablet:
VITAMINS
A (beta carotene) . . . . . . . . . . . . . . . . . . . . . . . . . . 2,840 IU 36% Daily Value
C (ascorbic acid) . . . . . . . . . . . . . . . . . . . . . . . . . . 120 mg 200% Daily Value
D (cholecalciferol) . . . . . . . . . . . . . . . . . . . . . . . . .840 IU 210% Daily Value
E (dl-alpha tocopheryl acetate) . . . . . . . . . . . . . .2 mg 7% Daily Value
B1 (thiamine mononitrate) . . . . . . . . . . . . . . . . . . .1.5 mg 88% Daily Value
B2 (riboflavin) . . . . . . . . . . . . . . . . . . . . . . . . . . . . . . .4 mg 200% Daily Value
Niacinamide . . . . . . . . . . . . . . . . . . . . . . . . . . . . . . . . 20 mg 100% Daily Value
B6 (pyridoxine hydrochloride) . . . . . . . . . . . . . . .50 mg 2000% Daily Value
Folic acid . . . . . . . . . . . . . . . . . . . . . . . . . . . . . . . . . . .1 mg 125% Daily Value
B12 (cyanocobalamin) . . . . . . . . . . . . . . . . . . . . . . 12 mcg 150% Daily Value
MINERALS
Calcium (calcium carbonate) . . . . . . . . . . . . . . . . 215 mg 17% Daily Value
Iron (as sodium iron EDTA and polysaccharide iron complex) . . .26 mg 144% Daily Value

Iodine . . . . . . . . . . . . . . . . . . . . . . . . . . . . . . . . 210 mcg 140% Daily Value
Magnesium (magnesium oxide) . . . . . . . . . . . . . 25 mg 6% Daily Value
Zinc (zinc oxide) . . . . . . . . . . . . . . . . . . . . . . . . . . . . 25 mg 167% Daily Value
Copper (cupric oxide) . . . . . . . . . . . . . . . . . . . . . . . .2 mg 100% Daily Value
Serving Size 1 Softgel:
at least 278 mg purified omega-3 fatty acids (as DHA, EPA, ALA, and DPA)
OTHER TABLET INGREDIENTS:
Microcrystalline Cellulose, Hydroxypropyl Methylcellulose, Crospovidone, Maltodextrin, Acacia Gum, Silicon Dioxide, Triacetin, Magnesium Stearate, Titanium Dioxide, Polydextrose, Yellow #6 Lake, Blue #2 Lake, Red #40 Lake.
OTHER SOFTGEL INGREDIENTS:
Ammonium Hydroxide, Ethylcellulose, Gelatin, Glycerin, Medium Chain Triglycerides, Oleic Acid, Sodium Alginate, Stearic Acid, Vanillin.
Softgel contains fish and soybeans

Directions:
Before, during and after pregnancy, one tablet and one enteric-coated softgel capsule taken by mouth daily, or as directed by a physician.
Use: To provide vitamin and mineral supplementation throughout pregnancy and during the postnatal period for both the lactating and non lactating mother. It is also useful for improving nutritional status prior to conception.

WARNINGS AND PRECAUTIONS

Warnings: Folic acid alone is improper therapy in the treatment of pernicious anemia and other megaloblastic anemias where Vitamin B12 is deficient.

Precautions: Folic acid especially in doses above 1.0 mg daily may obscure pernicious anemia (hematologic remission may occur while neurological manifestations remain progressive). Caution should be exercised to ensure that the prescribed dose of DHA does not exceed 1 gram (1,000 mg) per day. Since daily ingestion of more than 3 grams (3,000 mg) per day of omega-3 fatty acids (including alphalinolenic acid (ALA), eicosapentaenoic acid (EPA) and docosahexaenoic acid (DHA)) from fish oils may have potential antithrombotic activities and may increase bleeding times, administration of DHA should be avoided in patients with inherited or acquired bleeding diatheses, including those taking anticoagulants.

BOXED WARNING

WARNING: Accidental overdose of iron-containing products is a leading cause of fatal poisoning in children under 6. Keep this product out of reach of children. In case of accidental overdose, call a doctor or poison control center immediately.

STORAGE AND HANDLING

Store at room temperature

Keep out of reach of children

Manufactured for:

PruGen inc. Pharmaceuticals

8714 E Vista Bonita Dr

Scottsdale, AZ 85255